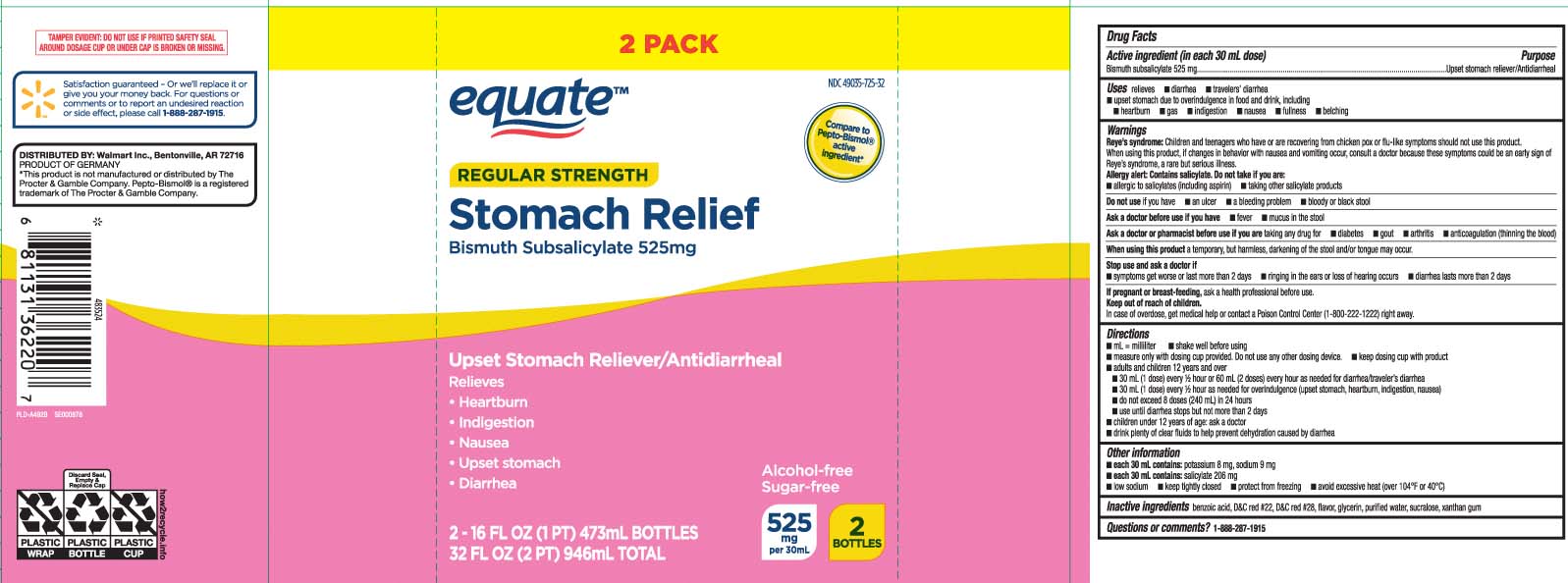 DRUG LABEL: Stomach Relief
NDC: 49035-725 | Form: LIQUID
Manufacturer: EQUATE (Wal-Mart Stores, Inc.) (see also WAL-MART INC)
Category: otc | Type: HUMAN OTC DRUG LABEL
Date: 20251216

ACTIVE INGREDIENTS: BISMUTH SUBSALICYLATE 525 mg/30 mL
INACTIVE INGREDIENTS: BENZOIC ACID; D&C RED NO. 22; D&C RED NO. 28; GLYCERIN; WATER; SUCRALOSE; XANTHAN GUM

Drug Facts

Active ingredient (in each 30 mL)

Bismuth subsalicylate 525 mg

Purpose

Upset stomach reliever/Antidiarrheal

Uses

relieves

- travelers' diarrhea
- diarrhea
- upset stomach due to overindulgence in food and drink, including:
  - heartburn
  - indigestion
  - nausea
  - gas
  - fullness
  - belching

Warnings

Reye's syndrome: Children and teenagers who have or are recovering from chicken pox or flu-like symptoms ahould not use this product. When using this product, if changes in behavior with nausea and vomiting occur, consult a doctor because these symptoms could be an early sign of Reye's syndrome, a rare but serious illness.

Allergy alert: Contains salicylate. Do not take if you are

- allergic to salicylates (including aspirin)
- taking other salicylate products

Do not use

if you have

- an ulcer
- a bleeding problem
- bloody or black stool

Ask a doctor before use if you have

- fever
- mucus in the stool

Ask a doctor or pharmacist before use if you are

taking any drug for

- diabetes
- gout
- arthritis
- anticoagulation (thinning the blood)

When using this product

a temporary, but harmless, darkening of the stool and/or tongue may occur.

Stop use and ask a doctor if

- symptoms get worse or last more than 2 days
- ringing in the ears or loss of hearing occurs
- diarrhea lasts more than 2 days

If pregnant or breast-feeding,

ask a health professional before use.

Keep out of reach of childen.

In case of overdose, get medical help or contact a Poison Control Center (1-800-222-1222) right away.

Directions

- mL = milliliter
- shake well before using
- measure only with dosing cup provided. do not use any other dosng device.
- keep dosing cup with product
- adults and children 12 years and over
  - 30 mL (1 dose) every 1/2 or 60 mL (2 doses) every hour as needed for diarrhea/traveler's diarrhea
  - 30 mL (1 dose) every 1/2 as needed for overindulgence (upset stomach, heartburn, indigestion, nausea)
  - do not exceed 8 doses (240 mL) in 24 hours
  - use until diarrhea stops but not more than 2 days
- children under 12 years of age: ask a doctor
- drink plenty of clear fluids to help prevent dehydration caused by diarrhea

Other information

- each 30 mL contains: potassium 8 mg sodium 9 mg
- each 30 mL contains: salicylate 206 mg
- low sodium
- keep tightly closed
- protect from freezing
- avoid excessive heat (over 104ºF or 40ºC)

Inactive ingredients

benzoic acid, D&C red #22, D&C red #28, flavor, glycerin, purified water, sucralose, xanthan gum

Questions or comments?

Call 1-888-287-1915

Principal Display Panel

Compare to Pepto-Bismol® active ingredient*

Regular Strength

Stomach Relief

Bismuth subsalicylate 525 mg

Upset Stomach Reliever/

Antidiarrheal

Relieves

- Heartburn
- Indigestion
- Nausea
- Upset stomach
- Diarrhea

Alcohol free

Sugar free

FL OZ (mL)

*This product is not manufactured or distributed by The Procter & Gamble Company. Pepto-Bismol® is a registered trademark of The Procter & Gamble Company.

TAMPER EVIDENT; DO NOT USE IF PRINTED SAFETY SEAL AROUND DOSAGE CUP OR UNDER CAP IS BROKEN OR MISSING.

DISTRIBUTED BY: Walmart Inc.,

Bentonville, AR 72716

Package Label

EQUATE Regular Strength Stomach Relief